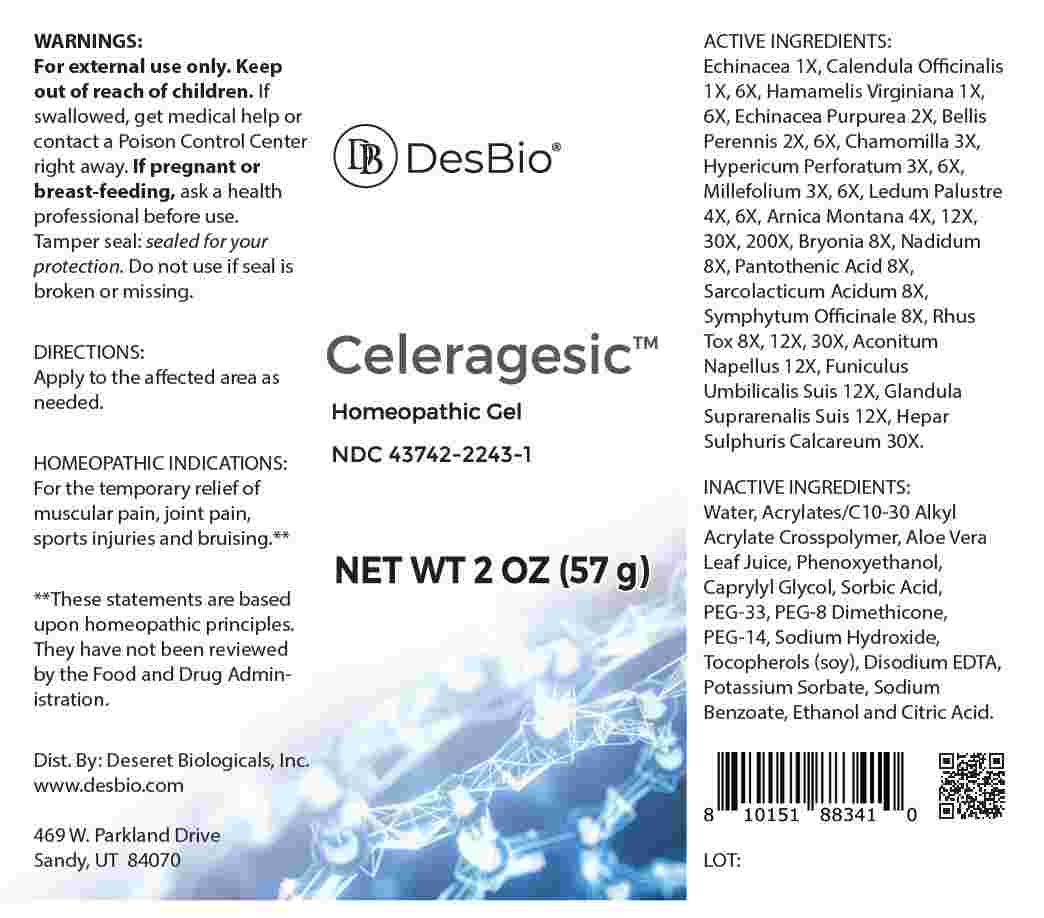 DRUG LABEL: Celeragesic
NDC: 43742-2243 | Form: GEL
Manufacturer: Deseret Biologicals, Inc.
Category: homeopathic | Type: HUMAN OTC DRUG LABEL
Date: 20250114

ACTIVE INGREDIENTS: ECHINACEA ANGUSTIFOLIA WHOLE 1 [hp_X]/1 g; CALENDULA OFFICINALIS FLOWERING TOP 1 [hp_X]/1 g; HAMAMELIS VIRGINIANA ROOT BARK/STEM BARK 1 [hp_X]/1 g; ECHINACEA PURPUREA WHOLE 2 [hp_X]/1 g; BELLIS PERENNIS WHOLE 2 [hp_X]/1 g; MATRICARIA CHAMOMILLA WHOLE 3 [hp_X]/1 g; HYPERICUM PERFORATUM WHOLE 3 [hp_X]/1 g; ACHILLEA MILLEFOLIUM WHOLE 3 [hp_X]/1 g; RHODODENDRON TOMENTOSUM LEAFY TWIG 4 [hp_X]/1 g; ARNICA MONTANA WHOLE 4 [hp_X]/1 g; BRYONIA ALBA ROOT 8 [hp_X]/1 g; NADIDE 8 [hp_X]/1 g; PANTOTHENIC ACID 8 [hp_X]/1 g; LACTIC ACID, L- 8 [hp_X]/1 g; COMFREY ROOT 8 [hp_X]/1 g; TOXICODENDRON PUBESCENS LEAF 8 [hp_X]/1 g; ACONITUM NAPELLUS WHOLE 12 [hp_X]/1 g; SUS SCROFA UMBILICAL CORD 12 [hp_X]/1 g; SUS SCROFA ADRENAL GLAND 12 [hp_X]/1 g; CALCIUM SULFIDE 30 [hp_X]/1 g
INACTIVE INGREDIENTS: WATER; PHENOXYETHANOL; CAPRYLYL GLYCOL; SORBIC ACID; ACRYLATES/C10-30 ALKYL ACRYLATE CROSSPOLYMER (60000 MPA.S AT 0.5%); POLYETHYLENE GLYCOL 1600; PEG-8 DIMETHICONE (600 CST); POLYETHYLENE GLYCOL 700; ALOE VERA LEAF; SODIUM HYDROXIDE; TOCOPHEROL; EDETATE DISODIUM; POTASSIUM SORBATE; ALCOHOL; SODIUM BENZOATE; CITRIC ACID MONOHYDRATE

DRUG FACTS:

ACTIVE INGREDIENTS:

Echinacea 1X, Calendula Officinalis 1X, 6X, Hamamelis Virginiana 1X, 6X, Echinacea Purpurea 2X, Bellis Perennis 2X, 6X, Chamomilla 3X, Hypericum Perforatum 3X, 6X, Millefolium 3X, 6X, Ledum Palustre 4X, 6X, Arnica Montana 4X, 12X, 30X, 200X, Bryonia 8X, Nadidum 8X, Pantothenic Acid 8X, Sarcolacticum Acidum 8X, Symphytum Officinale 8X, Rhus Tox 8X, 12X, 30X, Aconitum Napellus 12X, Funiculus Umbilicalis Suis 12X, Glandula Suprarenalis Suis 12X, Hepar Sulphuris Calcareum 30X.

PURPOSE:

For the temporary relief of muscular pain, joint pain, sports injuries and bruising.**

**These statements are based upon homeopathic principles. They have not been reviewed by the Food and Drug Administration.

WARNINGS:

For external use only. Keep out of reach of children. If swallowed, get medical help or contact a Poison Control Center right away.

If pregnant or breast-feeding, ask a health professional before use.

Tamper seal: sealed for your protection. Do not use if seal is broken or missing.

KEEP OUT OF REACH OF CHILDREN:

If swallowed, get medical help or contact a Poison Control Center right away.

DIRECTIONS:

Apply to the affected area as needed.

INDICATIONS:

For the temporary relief of muscular pain, joint pain, sports injuries and bruising.**

**These statements are based upon homeopathic principles. They have not been reviewed by the Food and Drug Administration.

INACTIVE INGREDIENTS:

Water, Acrylates/C10-30 Alkyl Acrylate Crosspolymer, Aloe Vera Leaf Juice, Phenoxyethanol, Caprylyl Glycol, Sorbic Acid, PEG-33, PEG-8 Dimethicone, PEG-14, Sodium Hydroxide, Tocopherols (soy), Disodium EDTA, Potassium Sorbate, Sodium Benzoate, Ethanol and Citric Acid.

QUESTIONS:

Dist. By: Deseret Biologicals, Inc.
www.desbio.com
469 W. Parkland Drive
Sandy, UT 84070

PACKAGE LABEL DISPLAY:

DesBio

Celeragesic

Homeopathic Gel

NDC 43742-2243-1

NET WT 2 OZ (57 g)